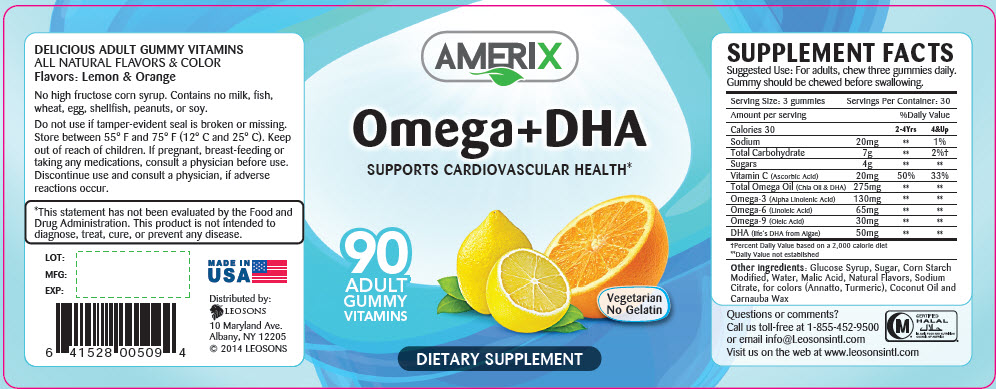 DRUG LABEL: Amerix Omega plus DHA
NDC: 69626-0509 | Form: TABLET, CHEWABLE
Manufacturer: Leosons Overseas Corporation
Category: other | Type: DIETARY SUPPLEMENT
Date: 20181107

ACTIVE INGREDIENTS: Sodium 6.66 mg/1 1; Ascorbic Acid 6.66 mg/1 1; Chia Seed Oil 91.66 mg/1 1; Linolenic Acid 43.33 mg/1 1; Linoleic Acid 21.66 mg/1 1; Oleic Acid 10 mg/1 1; Doconexent 16.66 mg/1 1; Sucrose 1.33 g/1 1
INACTIVE INGREDIENTS: Corn Syrup; Water; Malic acid; Annatto; Turmeric; Coconut Oil; Carnauba wax

AMERIX Omega + DHA

STATEMENT OF IDENTITY

SUPPLEMENT FACTS
Suggested Use: For adults, chew three gummies daily.
Gummy should be chewed before swallowing.
Serving Size: 3 gummies |  | Servings Per Container: 30
Amount per serving |  | %Daily Value
Calories 30 |  | 2-4Yrs | 4&Up
Sodium | 20mg | [Daily Value not established] | 1%
Total Carbohydrate | 7g |  | 2% [Percent Daily Value based on a 2,000 calorie diet]
Sugars | 4g
Vitamin C (Ascorbic Acid) | 20mg | 50% | 33%
Total Omega Oil (Chia Oil & DHA) | 275mg
Omega-3 (Alpha Linolenic Acid) | 130mg
Omega-6 (Linoleic Acid) | 65mg
Omega-9 (Oleic Acid) | 30mg
DHA (life's DHA from Algae) | 50mg

Other ingredients: Glucose Syrup, Sugar, Corn Starch Modified, Water, Malic Acid, Natural Flavors, Sodium Citrate, for colors (Annatto, Turmeric), Coconut Oil and Carnauba Wax

HEALTH CLAIM

DELICIOUS ADULT GUMMY VITAMINS

ALL NATURAL FLAVORS & COLOR

Flavors: Lemon & Orange

No high fructose corn syrup. Contains no milk, fish, wheat, egg, shellfish, peanuts, or soy.

Do not use if tamper-evident seal is broken or missing. Store between 55° F and 75° F (12° C and 25° C). Keep out of reach of children. If pregnant, breast-feeding or taking any medications, consult a physician before use. Discontinue use and consult a physician, if adverse reactions occur.

HEALTH CLAIM

*This statement has not been evaluated by the Food and Drug Administration. This product is not intended to diagnose, treat, cure, or prevent any disease.

Questions or comments?

Call us toll-free at 1-855-452-9500 or email info@Leosonsintl.com

Visit us on the web at www.leosonsintl.com

HEALTH CLAIM

CERTIFIED
HALAL
ISLAMIC FOOD AND NUTRITION
COUNCIL OF AMERICA

HEALTH CLAIM

LOT:
MFG:
EXP:

MADE IN USA

HEALTH CLAIM

Distributed by:
LEOSONS
10 Maryland Ave.
Albany, NY 12205
© 2014 LEOSONS

PRINCIPAL DISPLAY PANEL - 90 Tablet Bottle Label

AMERIX

Omega+DHA

SUPPORTS CARDIOVASCULAR HEALTH*

90
ADULT
GUMMY
VITAMINS

Vegetarian
No Gelatin

DIETARY SUPPLEMENT